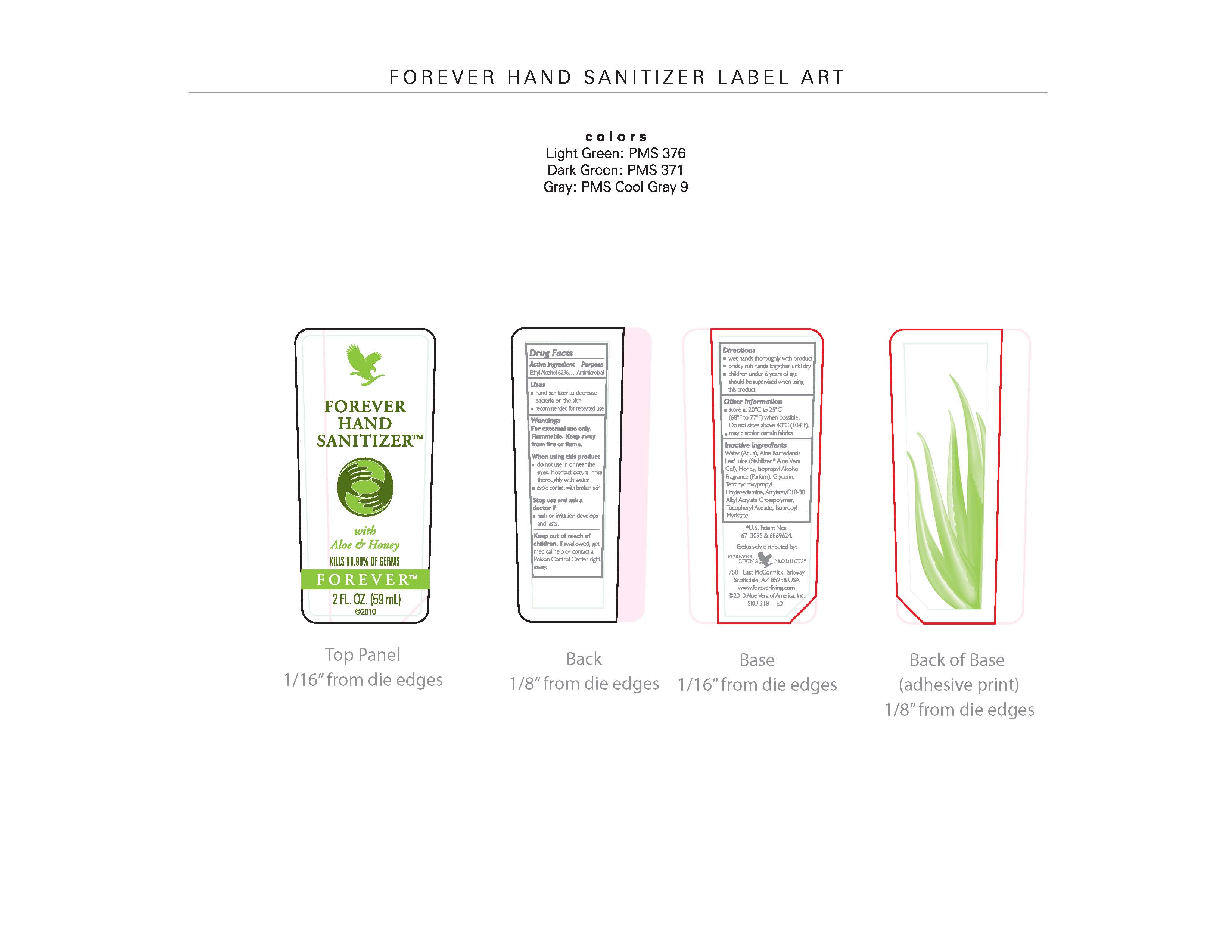 DRUG LABEL: Forever Hand Sanitizer
NDC: 11697-318 | Form: GEL
Manufacturer: Aloe Vera of America, Inc.
Category: otc | Type: HUMAN OTC DRUG LABEL
Date: 20100930

ACTIVE INGREDIENTS: Alcohol 36.58 mL/59 mL
INACTIVE INGREDIENTS: Water; Aloe Vera Leaf; Honey; Isopropyl Alcohol; LAVANDULA ANGUSTIFOLIA FLOWERING TOP; Cymbopogon Citratus Leaf; Glycerin; EDETOL; CARBOMER INTERPOLYMER TYPE A (55000 CPS); ALPHA-TOCOPHEROL ACETATE; Isopropyl Myristate

Drug Facts for an OTC drug listing SPL for Forever Hand Sanitizer

Active Ingredients

Active ingredient Purpose
Ethyl Alcohol 62%...Antimicrobial

Inactive Ingredients

Water (Aqua), Aloe Barbadensis Leaf Juice (Stabilized* Aloe Vera Gel), Honey, Isopropyl Alcohol, Fragrance (Parfum), Glycerin, Tetrahydroxypropyl, Ethylenediamine, Acrylates/C10-30 Alkyl Acrylate Crosspolymer, Tocopheryl Acetate, Isopropyl Myristate.

Purpose Section

Uses

- hand sanitizer to decrease bacteria on the skin
- recommended for repeated use

Warnings

Fore external use only.

Flammable. Keep away from fire or flame.

Indications & Usage

- do not use in or near the eyes. If contact occurs, rinse throughly with water.
- avoid contact with broken skin.

Stop use and ask a doctor if

- rash or irritation develops and lasts.

Keep out of reach of children. If swallowed, get medical help or contact a Poison Control Center right away.

Dosage & Administration Directions

Directions

- wet hands thoroughly with product
- briskly rub hands together until dry
- children under 6 years of age should be supervised when using this product

Other information

- store at 20°C to 25°C (68°F to 77°F) when possible. Do not store above 40°C (104° F).
- may discolor certain fabrics

Package Label Principal Display Panel

Label